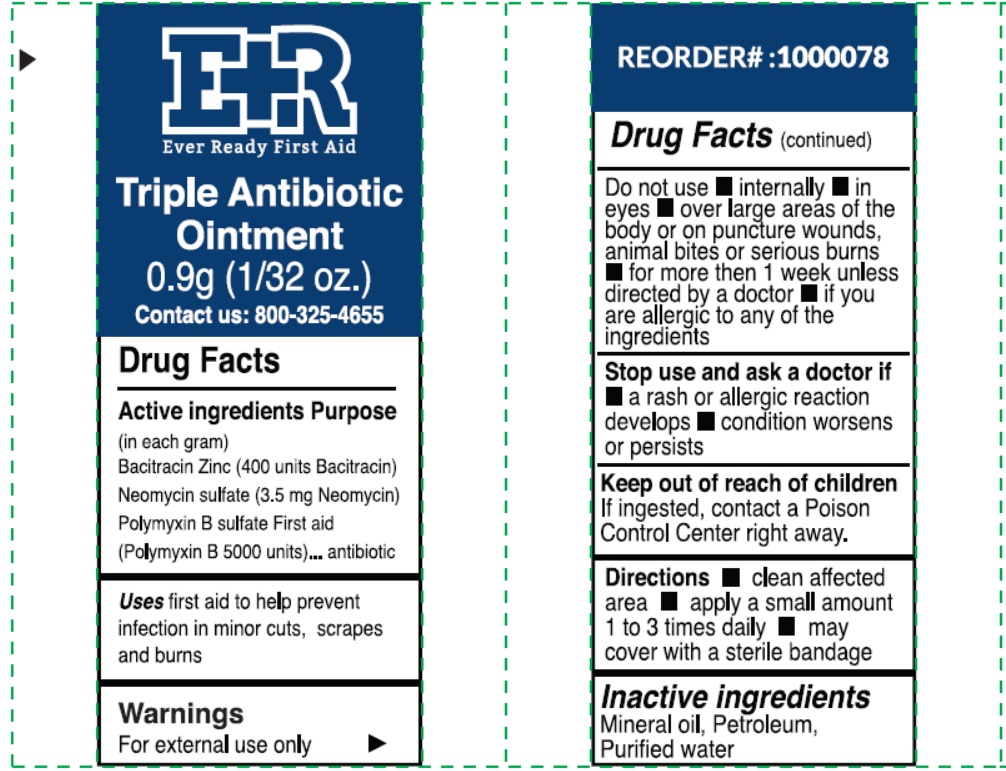 DRUG LABEL: Ever Ready First Aid Triple Antibiotic
NDC: 72976-009 | Form: OINTMENT
Manufacturer: EVER READY FIRST AID
Category: otc | Type: HUMAN OTC DRUG LABEL
Date: 20240115

ACTIVE INGREDIENTS: BACITRACIN ZINC 400 [USP'U]/1 g; NEOMYCIN SULFATE 0.0035 g/1 g; POLYMYXIN B SULFATE 5000 [USP'U]/1 g
INACTIVE INGREDIENTS: MINERAL OIL; PETROLATUM; WATER

Ever Ready First Aid
Triple Antibiotic Ointment

Active ingredients

(in each gram)
Bacitracin Zinc (400 units Bacitracin)
Neomycin sulfate (3.5 mg Neomycin)
Polymyxin B sulfate First aid
(Polymyxin B 5000 units)

Purpose

antibiotic

Uses

first aid to help prevent infection in minor cuts, scrapes and burns

Warnings

For external use only.

Do not use

- internally
- in eyes
- over large areas of the body or on puncture wounds, animal bites or serious burns
- for more then 1 week unless directed by a doctor
- if you are allergic to any of the ingredients

Stop use and ask a doctor if

- a rash or allergic reaction develops
- condition worsens or persists

Keep out of reach of children

If ingested, contact a Poison Control Center right away.

Directions

- clean affected area
- apply a small amount 1 to 3 times daily
- may cover with a sterile bandag

Inactive ingredients

Mineral oil, Petroleum, Purified water